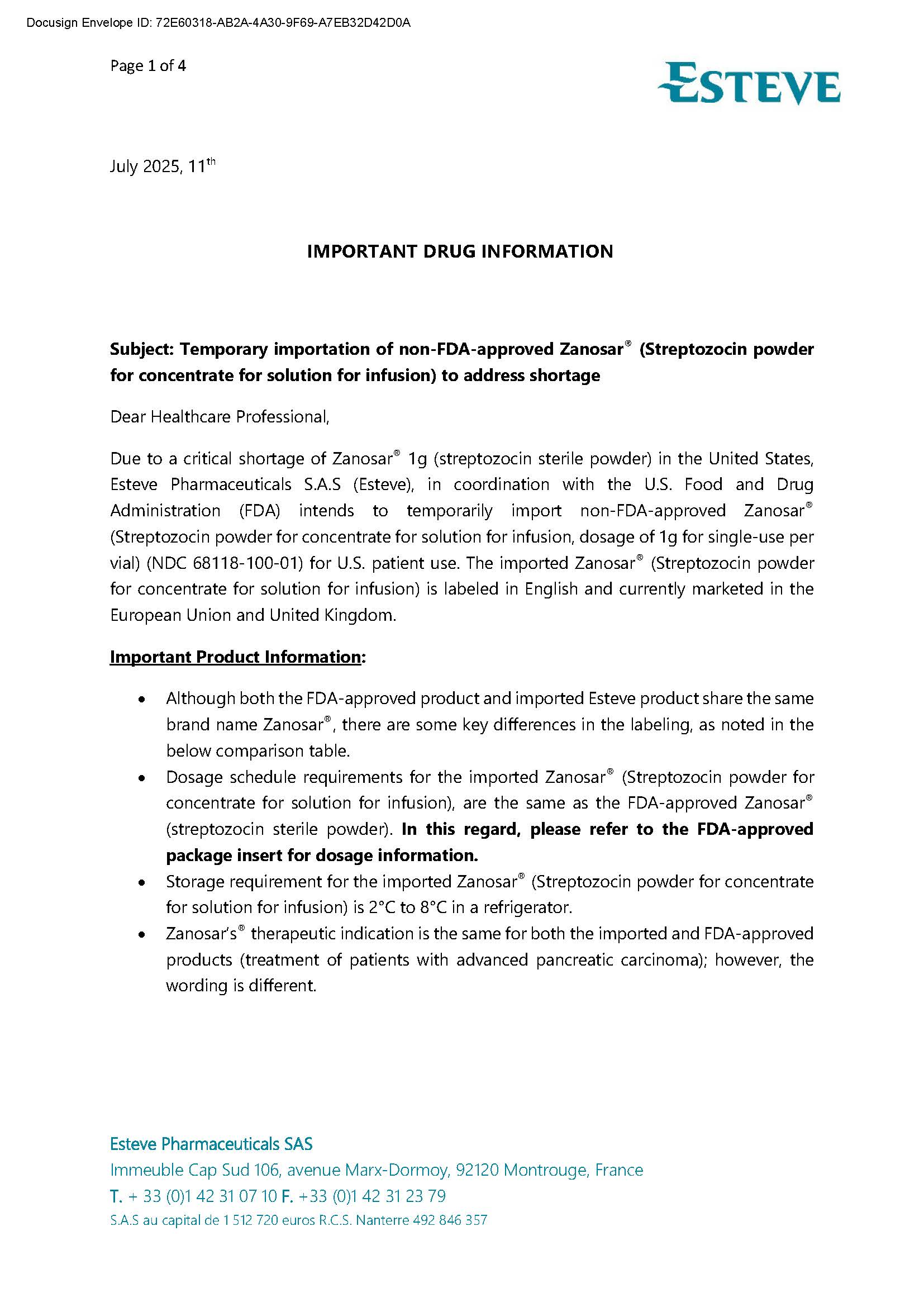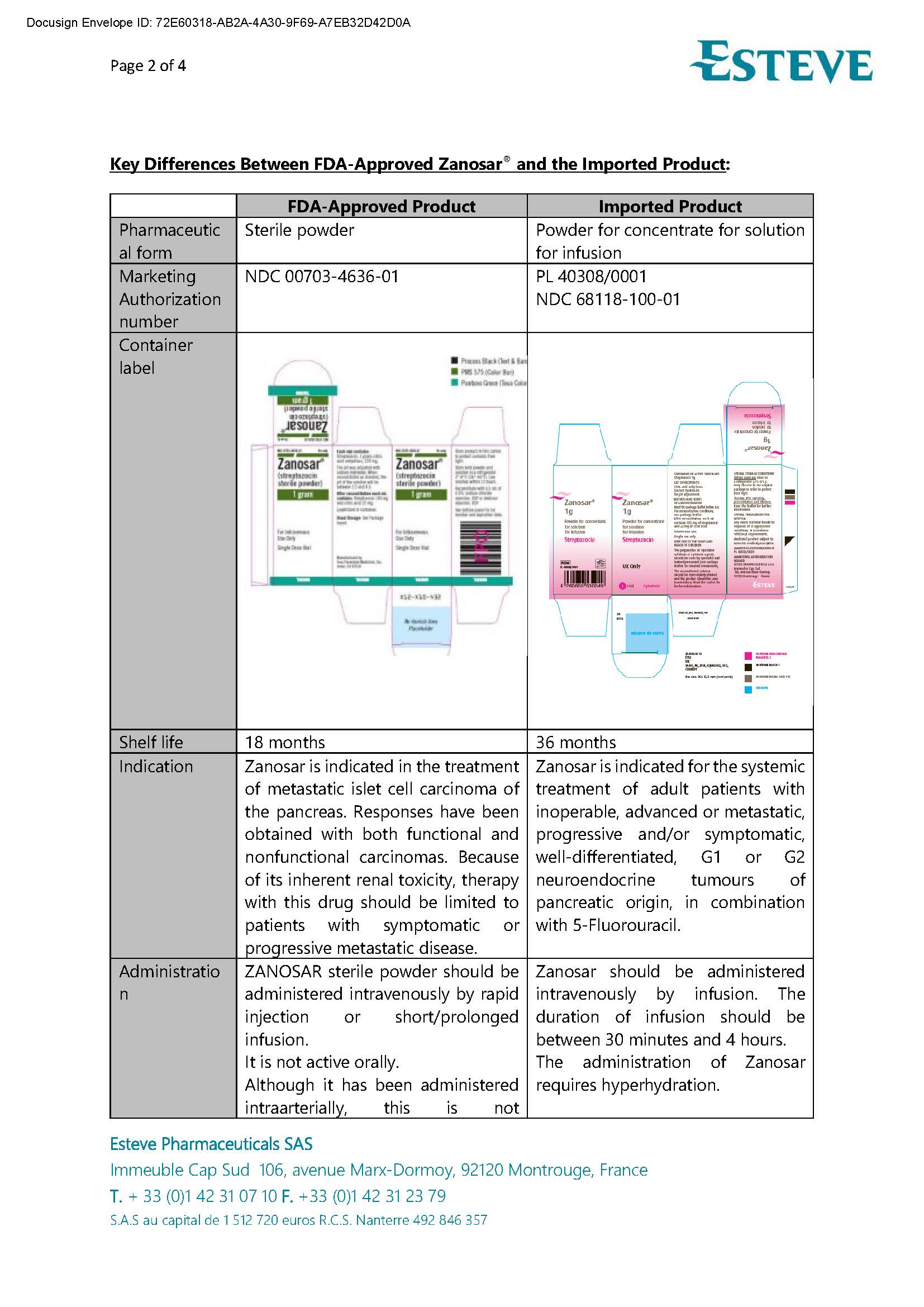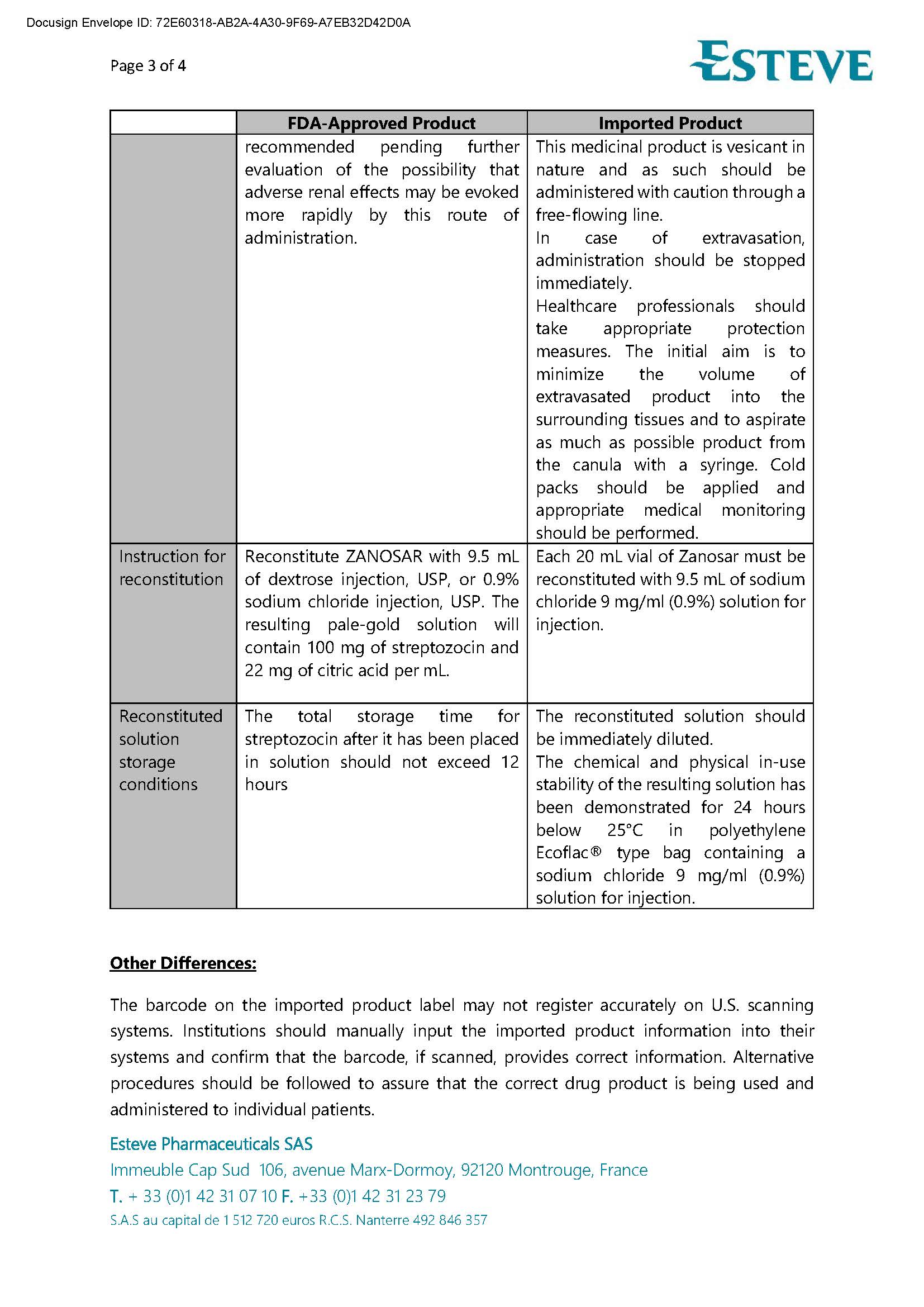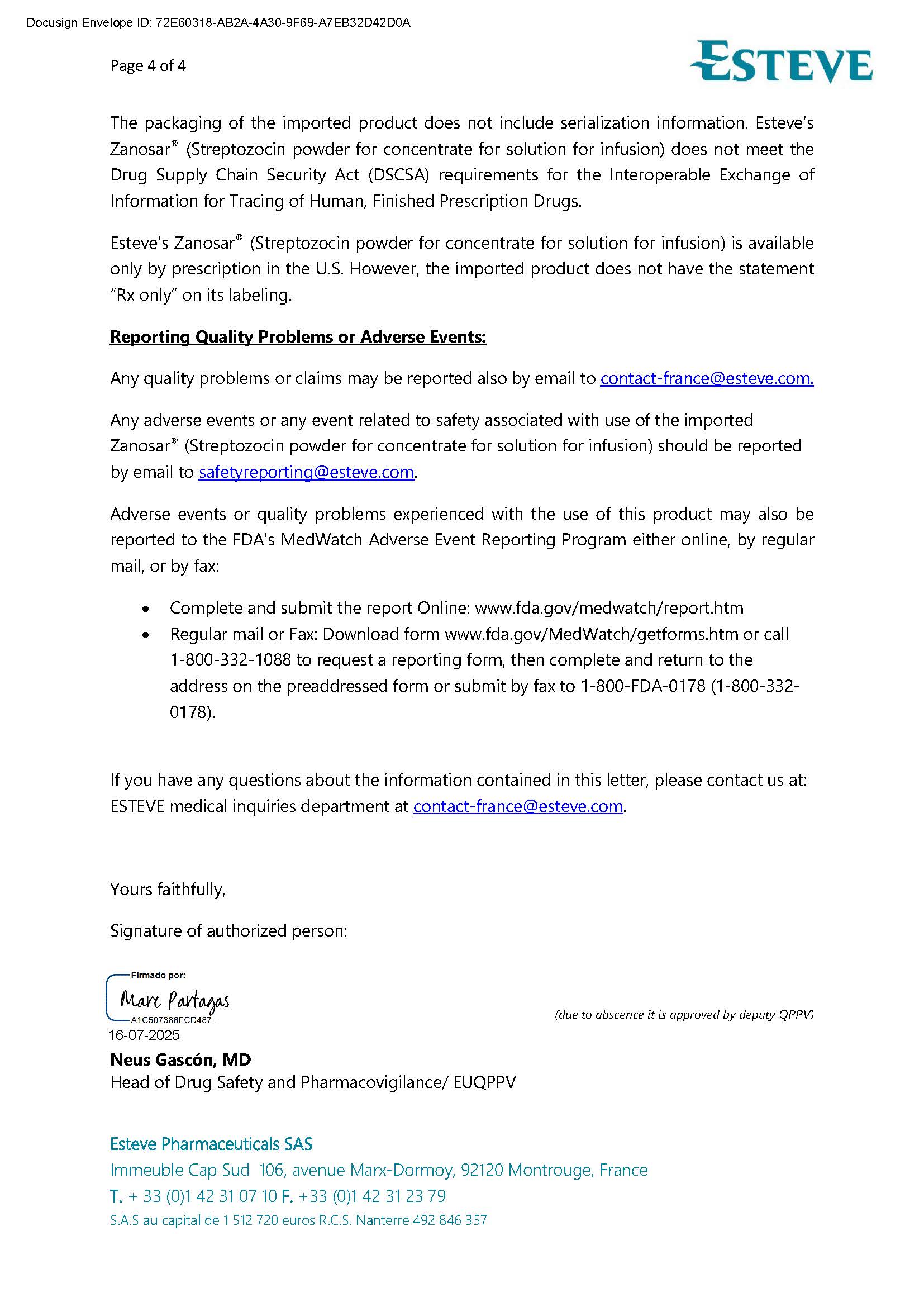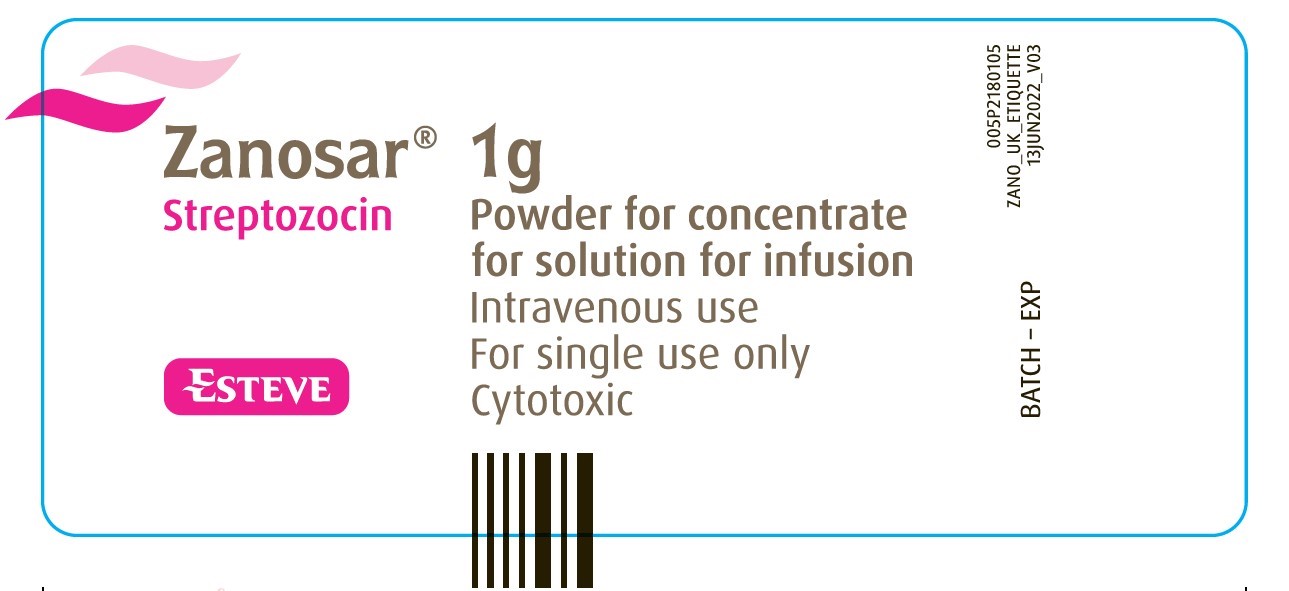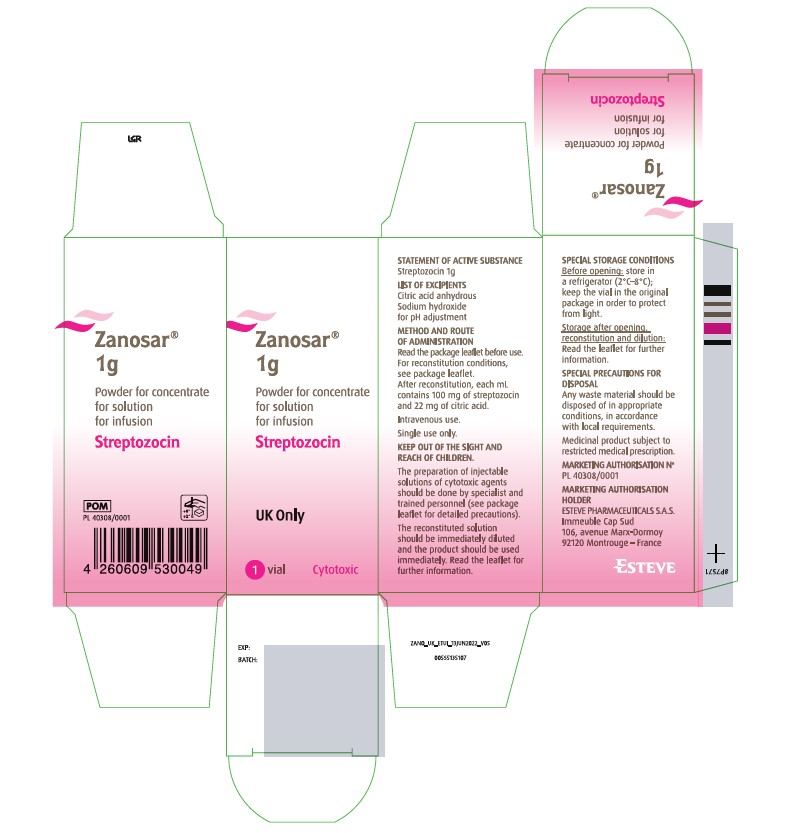 DRUG LABEL: Zanosar
NDC: 68118-100 | Form: POWDER, FOR SOLUTION
Manufacturer: ESTEVE PHARMACEUTICALS, S.A.
Category: prescription | Type: HUMAN PRESCRIPTION DRUG LABEL
Date: 20251006

ACTIVE INGREDIENTS: STREPTOZOCIN 1 g/10 mL
INACTIVE INGREDIENTS: SODIUM HYDROXIDE; ANHYDROUS CITRIC ACID

Zanosar (Streptozocin) powder, for injection

Dear Health Care Provider Letter

How supplied

NDC 68118-100-01: Each vial contains 1g Streptozocin Powder for concentrate for solution for infusion. Each carton contains 1 vial.

Vial Label

carton (box) label